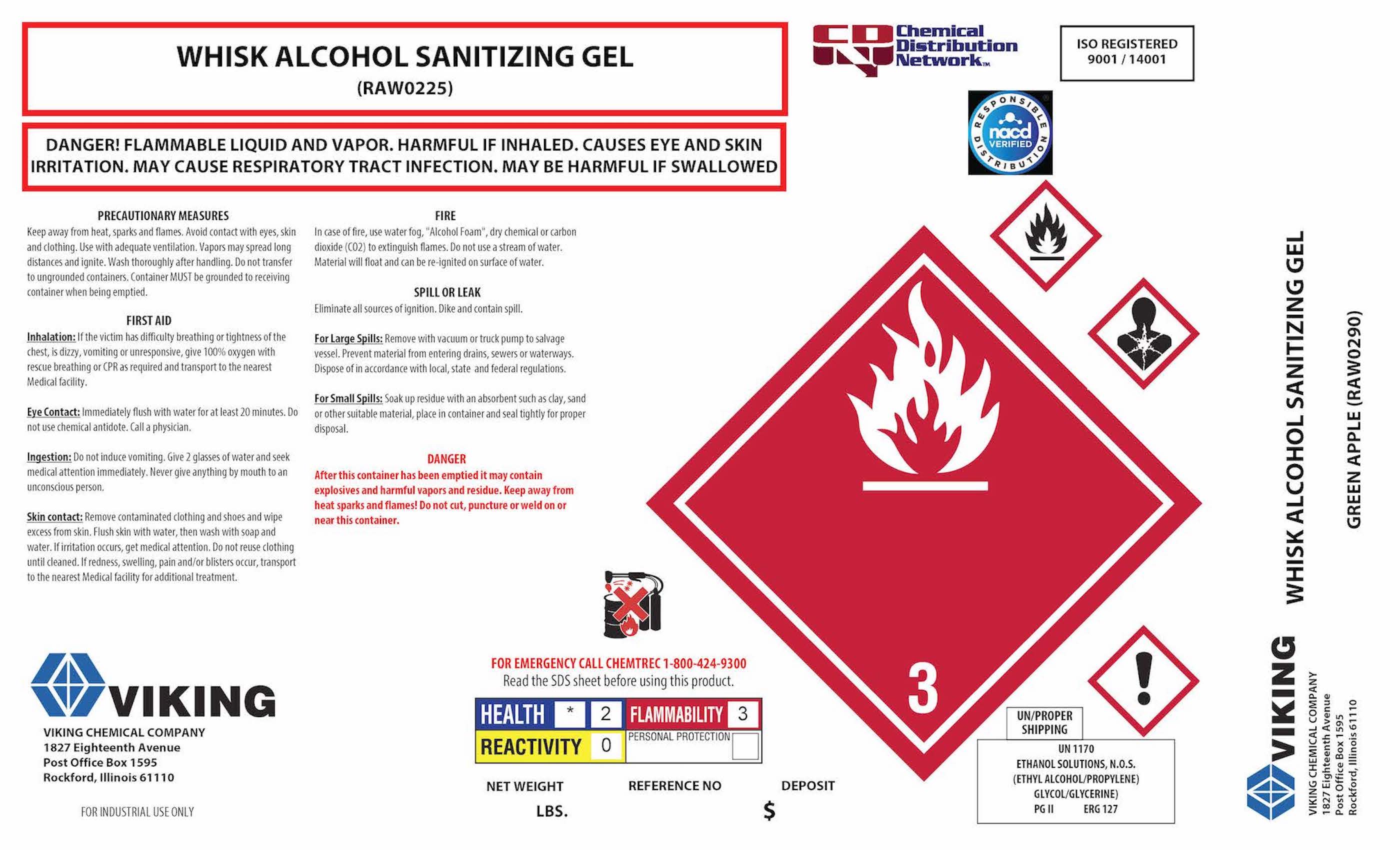 DRUG LABEL: Whisk Alcohol Sanitizing Gel
NDC: 74313-376 | Form: GEL
Manufacturer: Viking Chemical Company
Category: otc | Type: HUMAN OTC DRUG LABEL
Date: 20211214

ACTIVE INGREDIENTS: ALCOHOL 644.8 L/1041 L
INACTIVE INGREDIENTS: CARBOMER INTERPOLYMER TYPE A (ALLYL SUCROSE CROSSLINKED) 14.14 L/1041 L; WATER 376.38 L/1041 L; TROLAMINE 1.77 L/1041 L

Whisk Care WC 375

Active Ingredients

Alcohol 66% v/v. Purpose: Antiseptic

Purpose

Antiseptic, Hand Sanitizer

Indications and Use

Hand Sanitizer to help reduce bacteria that potentially can cause disease. For use when soap and water are not available.

Keep out of reach of children. If swallowed, get medical help or contact a Poison Control Center right away.

Directions

Place enough product on hands to cover all surfaces. Rub hands together until dry. Supervise children under 6 years of age when using this product to avoid swallowing.

Inactive Ingredients

deionized water, glycerine, propylene glycol

Warnings

For external use only. Flammable. Keep away from heat or flame.